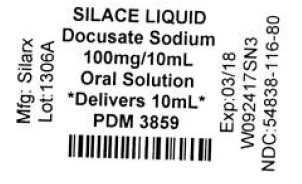 DRUG LABEL: Silace
NDC: 68151-0116 | Form: LIQUID
Manufacturer: Carilion Materials Management
Category: otc | Type: HUMAN OTC DRUG LABEL
Date: 20171228

ACTIVE INGREDIENTS: DOCUSATE SODIUM 10 mg/1 mL
INACTIVE INGREDIENTS: anhydrous citric acid; D&C red no. 33; methylparaben; propylene glycol; propylparaben; SODIUM CITRATE, UNSPECIFIED FORM; water; Poloxamer 407

Silace Liquid

Active Ingredient: Docusate sodium 10 mg (in each 1 mL)

Purpose: Stool Softener

Uses

- for gentle, reliable relief from occasional constipation (irregularity)
- generally produces bowel movement in 12 to 72 hours

Warning

- Do not use laxative products for longer than 1 week unless told to do so by a doctor
- if you are presently taking mineral oil unless told to do by a doctor

Ask doctor before use if you have

- stomach pain
- nausea
- vomiting
- noticed a sudden change in bowel habits that last over two weeks

Stop use and ask a doctor if you have rectal bleeding or fail to have a bowel movement after use of a laxative. These could be signs of a serious condition

PREGNANCY OR BREAST FEEDING

If pregnant or breast feeding, ask a health professional before use.

Keep out of reach of children. In case of overdose, get medical help or contact a Poison Control Center right away.

Directions

- take as indicated by doctor
- this product must be given in a 6 to 8 oz. glass of milk or fruit juice or infant's formula to prevent throat irritation. Dose may be taken as a single daily dose or in divided doses
- dosage should be adjusted to individual response
- higher doses are recommended for initial therapy
- the effect on stools is usually apparent 1 to 3 days after the first dose

Adults and children over 12 years | 50 to 200 mg (1 to 4 teaspoonful)
Children 6 to under 12 years | 50 to 100 mg (1 to 2 teaspoonful)
Children 3 to under 6 years | 25 to 50 mg(1/2 to 1 teaspoonful)
Children under 3 years of age | Ask a doctor

Other information

- store at room temperature 20°-25°C (68°-77°F)
- protect from freezing and excessive heat
- do not use if tamperevident safety seal around cap is broken or missing
- dispense in tight, light-resistant container with a child-resistant closure

Inactive ingredients

citric acid, D&C red no. 33, flavor, methylparaben, Poloxamer, propylene glycol, propylparaben, purified water, sodium citrate.

Questions

888-974-5279

This product is not manufactured or distributed by Purdue Products LP, distributor of Colace® Liquid.

Manufactured by:

Silarx Pharmaceuticals, Inc.
1033 Stoneleigh Ave
Carmel, NY 10512
USA

HOW SUPPLIED

Product: 68151-0116

NDC: 68151-0116-1 1 mL in a CUP, UNIT-DOSE